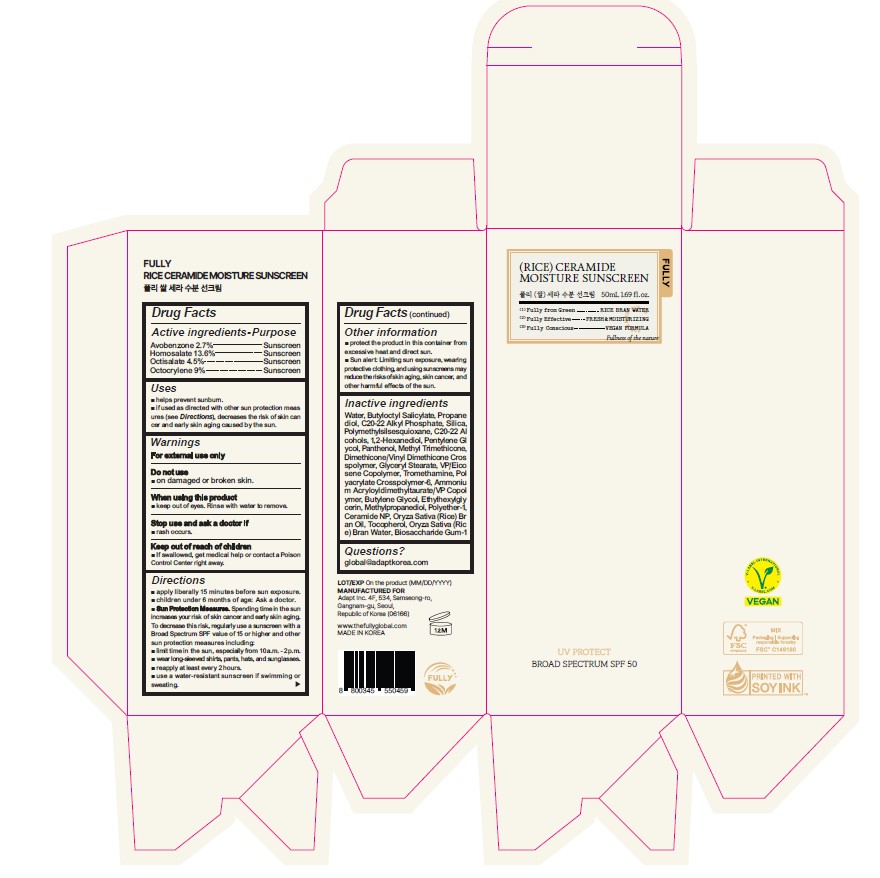 DRUG LABEL: FULLY RICE CERAMIDE MOISTURE SUNSCREEN
NDC: 87343-001 | Form: CREAM
Manufacturer: Adapt Inc.
Category: otc | Type: HUMAN OTC DRUG LABEL
Date: 20260224

ACTIVE INGREDIENTS: AVOBENZONE 27 mg/1 mL; HOMOSALATE 136 mg/1 mL; OCTISALATE 45 mg/1 mL; OCTOCRYLENE 90 mg/1 mL
INACTIVE INGREDIENTS: WATER; BUTYLOCTYL SALICYLATE; PROPANEDIOL; C20-22 ALKYL PHOSPHATE; SILICON DIOXIDE; POLYMETHYLSILSESQUIOXANE (4.5 MICRONS); C20-22 ALCOHOLS; 1,2-HEXANEDIOL; PENTYLENE GLYCOL; PANTHENOL; METHYL TRIMETHICONE; DIMETHICONE/VINYL DIMETHICONE CROSSPOLYMER (HARD PARTICLE); GLYCERYL MONOSTEARATE; VINYLPYRROLIDONE/EICOSENE COPOLYMER; TROMETHAMINE; AMMONIUM ACRYLOYLDIMETHYLTAURATE, DIMETHYLACRYLAMIDE, LAURYL METHACRYLATE AND LAURETH-4 METHACRYLATE COPOLYMER, TRIMETHYLOLPROPANE TRIACRYLATE CROSSLINKED (45000 MPA.S); AMMONIUM ACRYLOYLDIMETHYLTAURATE/VP COPOLYMER; BUTYLENE GLYCOL; ETHYLHEXYLGLYCERIN; METHYLPROPANEDIOL; POLYETHER-1 (2800 MPA.S); CERAMIDE NP; RICE BRAN OIL; TOCOPHEROL; RICE BRAN, DEFATTED; BIOSACCHARIDE GUM-1

87343-001_FULLY RICE CERAMIDE MOISTURE SUNSCREEN

Keep out of reach of children. If swallowed, get medical help or contact a Poison Control Center right away

ACTIVE INGREDIENT

Avobenzone 2.7%

Homosalate 13.6%

Octisalate 4.5%

Octocrylene 9.0%

PURPOSE

Sunscreen

INDICATIONS AND USAGE

Helps prevent sunburn
If used as directed with other sun protection measures (see Directions), decreases the risk of skin cancer and early skin aging caused by the sun.

WARNINGS

For external use only

Do not use on damaged or broken skin

When using this product, keep out of eyes. Rinse with water to remove.

Stop using and ask a doctor if rash occurs.

DOSAGE AND ADMINISTRATION

Apply liberally 15 minutes before sun exposure. Reapply at least every two hours

Use a water-resistant sunscreen if swimming or sweating

Sun protection measures. Spending time in the sun increases your risk of skin cancer and early skin aging. To decrease this risk, regularly use a sunscreen with a broad spectrum SPF of 15 or higher and other sun protection measures including: - Limit time in the sun, especially from 10 am to 2 pm. - Wear long-sleeve shirts, pants, hats, and sunglasses

Children under 6 months of age: Ask a doctor

INACTIVE INGREDIENT

WATER, BUTYLOCTYL SALICYLATE, PROPANEDIOL, C20-22 ALKYL PHOSPHATE, SILICA, POLYMETHYLSILSESQUIOXANE, C20-22 ALCOHOLS, 1,2-HEXANEDIOL, PENTYLENE GLYCOL, PANTHENOL, METHYL TRIMETHICONE, DIMETHICONE/VINYL DIMETHICONE CROSSPOLYMER, GLYCERYL STEARATE, VP/EICOSENE COPOLYMER, TROMETHAMINE, POLYACRYLATE CROSSPOLYMER-6, AMMONIUM ACRYLOYLDIMETHYLTAURATE/VP COPOLYMER, BUTYLENE GLYCOL, ETHYLHEXYLGLYCERIN, METHYLPROPANEDIOL, POLYETHER-1, CERAMIDE NP, ORYZA SATIVA (RICE) BRAN OIL, TOCOPHEROL, ORYZA SATIVA (RICE) BRAN WATER, BIOSACCHARIDE GUM-1

OTHER SAFETY INFORMATION

Protect the product in the container from excessive heat and direct sun